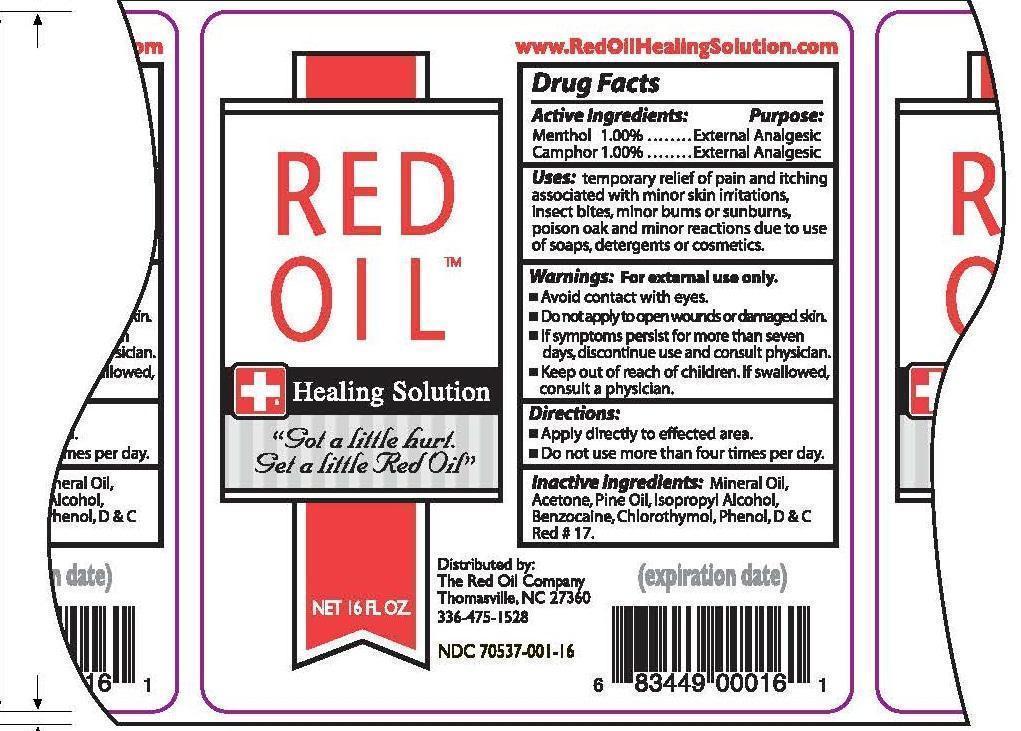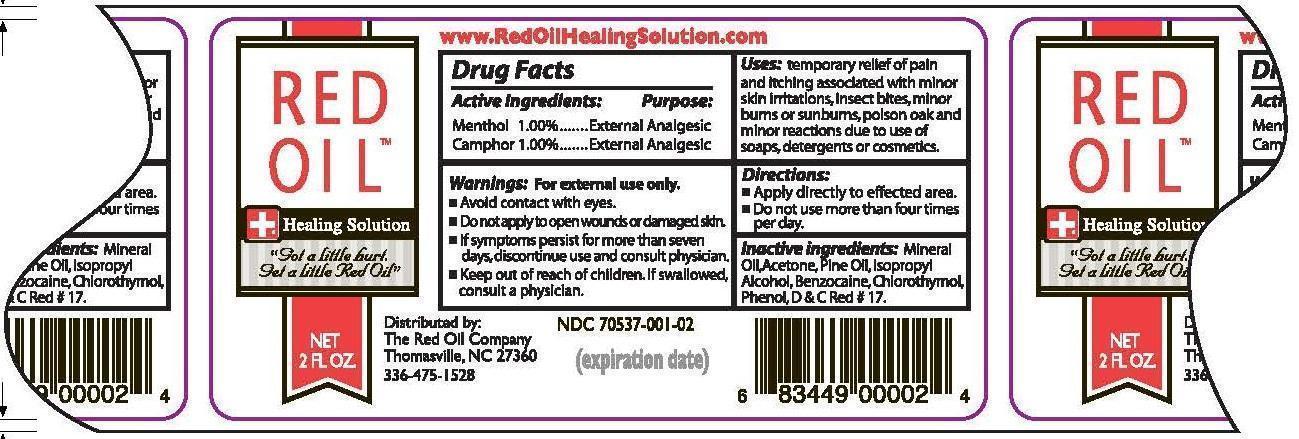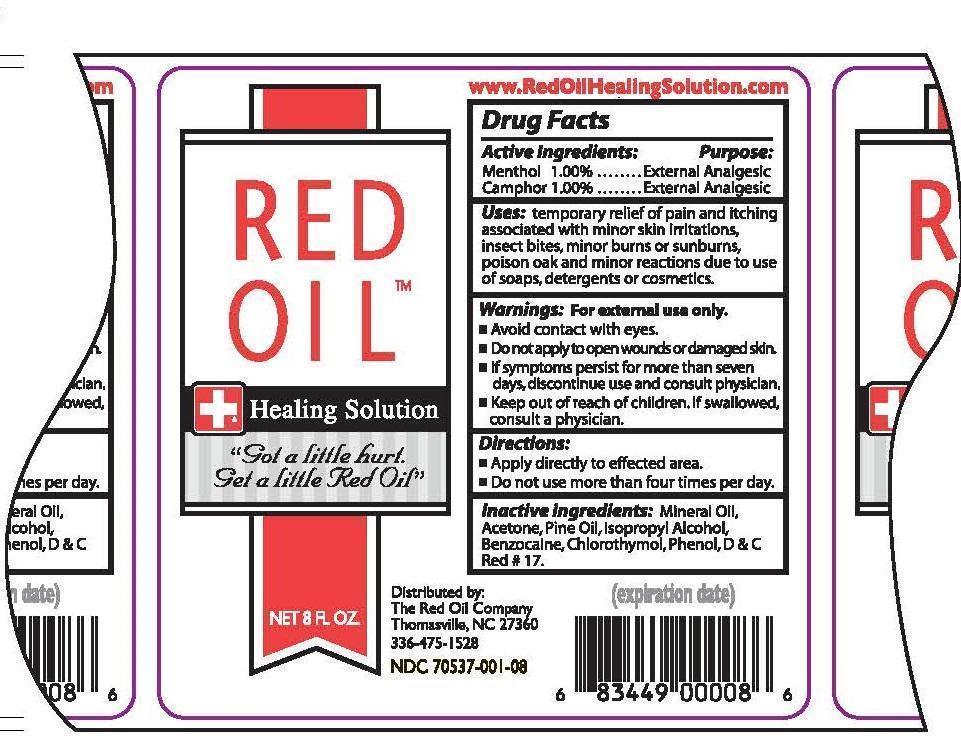 DRUG LABEL: Red Oil
NDC: 70537-001 | Form: OIL
Manufacturer: The Red Oil Company
Category: otc | Type: HUMAN OTC DRUG LABEL
Date: 20200124

ACTIVE INGREDIENTS: MENTHOL 10 mg/1 mL; CAMPHOR (SYNTHETIC) 10 mg/1 mL
INACTIVE INGREDIENTS: MINERAL OIL; ACETONE; WHITE PINE OIL; ISOPROPYL ALCOHOL; BENZOCAINE; CHLOROTHYMOL; PHENOL

Actives

Camphor 1 %

Menthol 1%

Purpose

External Analgesic

Indication

Temporary relief from pain and itiching associated with minor skin irritations , insect bites, minor burns or sun burns, posion oak and minor reactions due to use of soaps, detergents or cosmetics.

Directions

Apply directly to affected area

Do not use more than four times per day